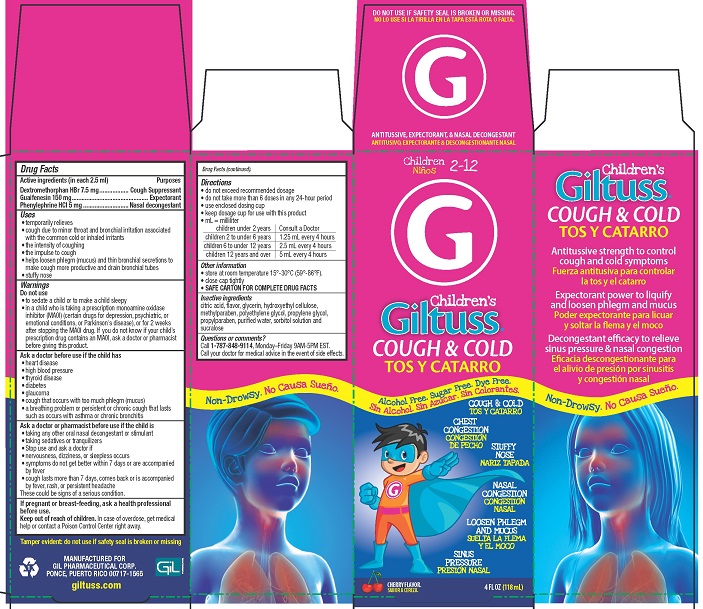 DRUG LABEL: Giltuss Childrens Cough and Cold
NDC: 58552-131 | Form: SOLUTION
Manufacturer: Gil Pharmaceutical Corp
Category: otc | Type: HUMAN OTC DRUG LABEL
Date: 20251009

ACTIVE INGREDIENTS: DEXTROMETHORPHAN HYDROBROMIDE 7.5 mg/2.5 mL; GUAIFENESIN 150 mg/2.5 mL; PHENYLEPHRINE HYDROCHLORIDE 5 mg/2.5 mL
INACTIVE INGREDIENTS: WATER; POLYETHYLENE GLYCOL, UNSPECIFIED; SORBITOL; SUCRALOSE; ANHYDROUS CITRIC ACID; PROPYLPARABEN; PROPYLENE GLYCOL; METHYLPARABEN; HYDROXYETHYL CELLULOSE (2000 MPA.S AT 1%); GLYCERIN

Giltuss Children's Cough & Cold

Drug Facts

Active ingredients (in each 2.5 mL)

Dextromethorphan HBr 7.5 mg

Guaifenesin 150 mg

Phenylephrine HCI 5 mg

Purposes

Cough Suppressant

Expectorant

Nasal decongestant

Uses

- temporarily relieves
- cough due to minor throat and bronchial irritation associated with the common cold or inhaled irritants
- the intensity of coughing
- the impulse to cough
- helps loosen phlegm (mucus) and thin bronchial secretions to make cough more productive and drain bronchial tubes
- stuffy nose

Warnings

Do not use

- to sedate a child or make a child sleepy
- in a child who is taking a prescription monoamine oxidase inhibitor (MAOI) (certain drugs for depression, psychiatric, or emotional conditions, or Parkinson's disease), or for 2 weeks after stopping the MAOI drug. If you do not know if your child's prescription drug contains an MAOI, ask a doctor or pharmacist before giving this product.

Ask a doctor before use if the child has

- heart disease
- high blood pressure
- thyroid disease
- diabetes
- glaucoma
- cough that occurs with too much phlegm (mucus)
- a breathing problem or persistent or chronic cough that lasts such as occurs with asthma or chronic bronchitis

Ask a doctor or pharmacist before use if the child is

- taking any other oral nasal decongestant or stimulant
- taking sedatives, tranquilizers

- Stop use and ask a doctor if
- nervousness, dizziness, or sleepless occurs
- symptoms do not get better within 7 days or are accompanied by fever
- cough lasts more than 7 days, comes back, or occurs with fever, rash or persistant headache

These can be signs of a serious condition.

PREGNANCY OR BREAST FEEDING

If pregnant or breast-feeding, ask a health professional before use.

Keep out of reach of children.In case of overdose, get medical help or contact a Poison Control Center right away.

Directions

- do not exceed recommended dosage
- do not take more than 6 doses in any 24 hour period
- keep dosing cup for use with this product
- mL = milliliters

children under 2 years | Consult a doctor
children 2 to under 6 years of age | 1.25 mL every 4 hours
children 6 to 12 years of age | 2.5 mL every 4 hours
children 12 years and over | 5 mL every 4 hours

Other information

- store at room temperature 15°- 30°C (59° - 86°F)
- close cap tightlly
- SAVE CARTON FOR COMPLETE DRUG FACTS

Inactive ingredients

citric acid, flavor, glycerin, hydroxyethylcellulose, methylparaben, polyethylene glycol, propylene glycol, propylparaben, purified water, sorbitol solution, and sucralose.

Questions or comments?

Call 1-787-848-9114, Monday - Friday 9AM - 5PM EST. Call your doctor for medical advice in the event of side effects.

Tamper evident: do not use if safety seal is broken or missing

MANUFACTURED FOR

GIL PHARMACEUTICAL CORP.

PONCE, PUERTO RICO 00717-1565

PACKAGE LABEL

Children's

GILTUSS®

COUGH & COLD

ANTITUSSIVE, EXPECTORANT, NASAL DECONGESTANT

Alcohol Free. Sugar Free. Dye Free.

- COUGH AND COLD
- CHEST CONGESTION
- STUFFY NOSE
- NASAL CONGESTION
- LOOSEN PHLEGM AND MUCUS
- SINUS PRESSURE

CHERRY FLAVOR

4 FL OZ (118 mL)